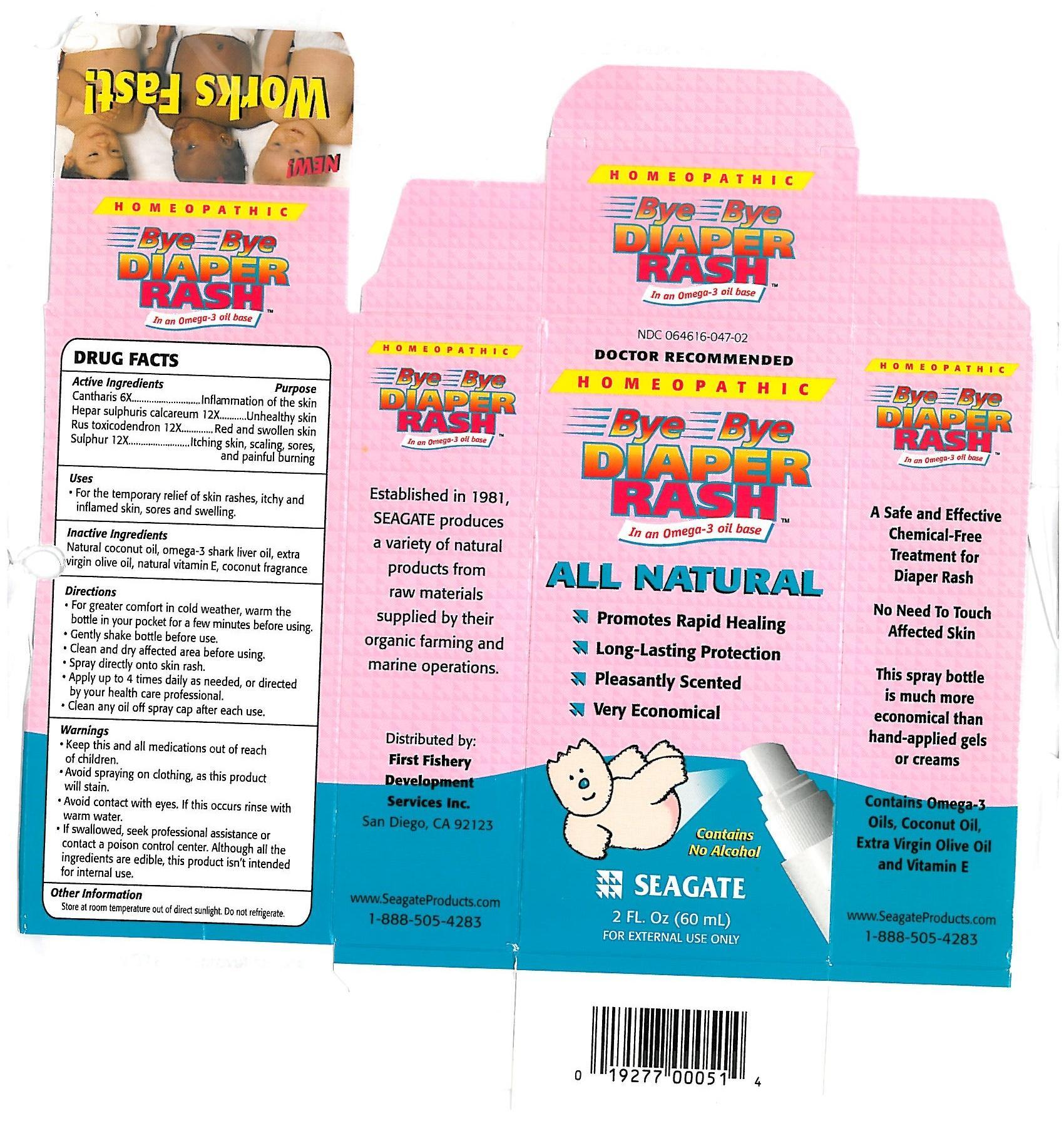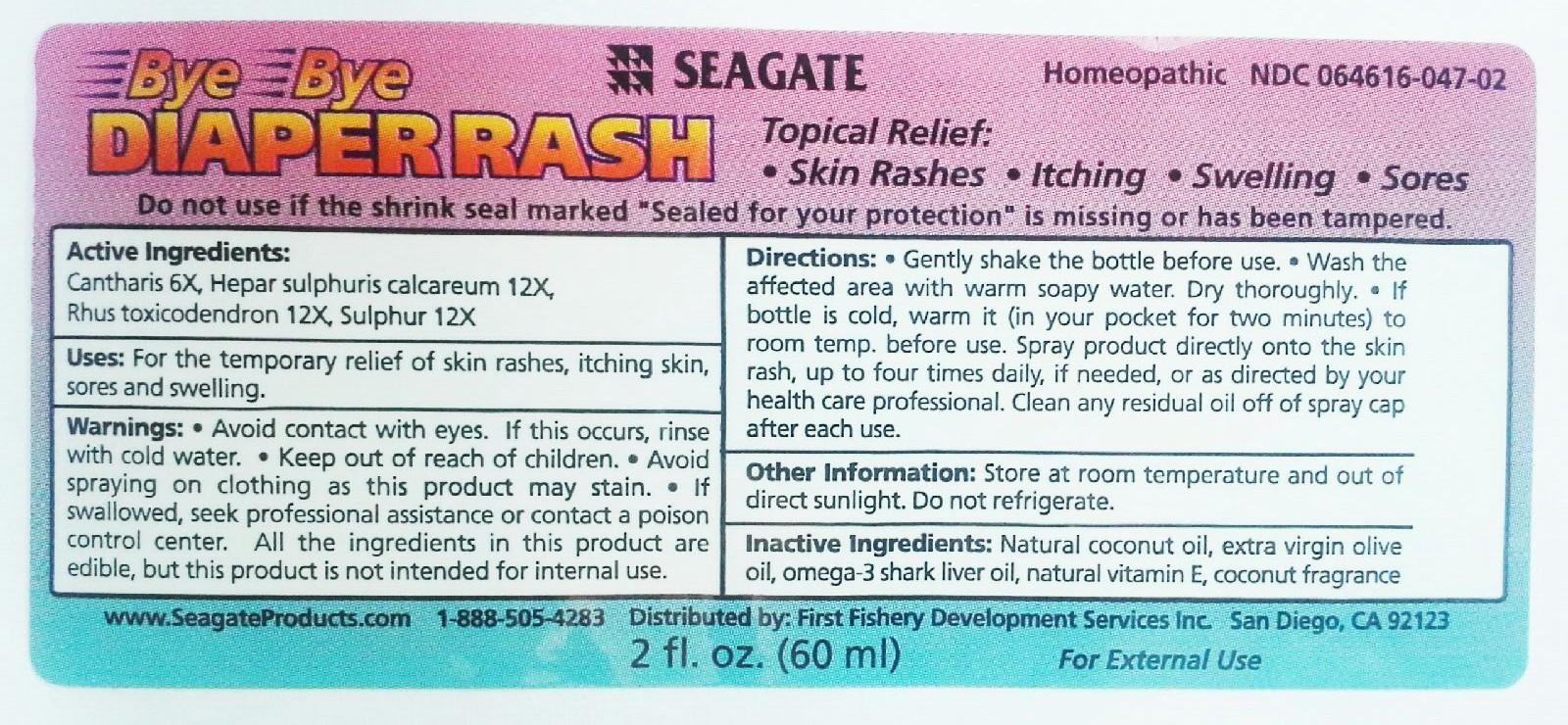 DRUG LABEL: Bye Bye Diaper Rash
NDC: 64616-047 | Form: LIQUID
Manufacturer: Vitality Works, Inc.
Category: homeopathic | Type: HUMAN OTC DRUG LABEL
Date: 20171204

ACTIVE INGREDIENTS: SULFUR 12 [hp_X]/1 mL; CALCIUM SULFIDE 12 [hp_X]/1 mL; TOXICODENDRON PUBESCENS LEAF 12 [hp_X]/1 mL; LYTTA VESICATORIA 6 [hp_X]/1 mL
INACTIVE INGREDIENTS: COCONUT OIL; SHARK LIVER OIL; OLIVE OIL; ALPHA-TOCOPHEROL

Bye Bye Diaper Rash

Bye Bye Diaper Rash

Cantharis 6X

Hepar sulphuris calcareum 12X

Rus toxicodendron 12X

Sulphur 12X

Bye Bye Diaper Rash

Natural coconut oil, omega-3 shark liver oil, extra virgin olive oil, natural vitamin E, coconut fragrance.

Bye Bye Diaper Rash

Keep this and all medicines out of reach of children. Avoid spraying on clothing as this product will stain. Avoid contact with eyes. If this occurs rinse with warm water. If swallowed, seek professional assistance or contact a poison control center. Although all the ingredients are edible, this product isn't intended for internal use.

Bye Bye Diaper Rash

Keep this and all medications out of reach of children.

Bye Bye Diaper Rash

For the temporary relief of skin rashes, itchy and inflamed skin, sore and swelling.

Bye Bye Diaper Rash

For greater comfort in cold weather, warm the bottle in your pocket for a few minutes before using. Gently shake bottle before use. Clean and dry affected area before using. Spray directly onto skin rash. Apply up to 4 times daily as needed or directed by your health care professional. Clean any oil off spray cap after each use.

Bye Bye Diaper Rash

Cantharis - for inflammation of the skin.

Hepar sulphuris calcareum - for unhealthy skin.

Rus toxicodendron - for red and swollen skin.

Sulphur - for itching skin, scaling, sores, and painful buring.